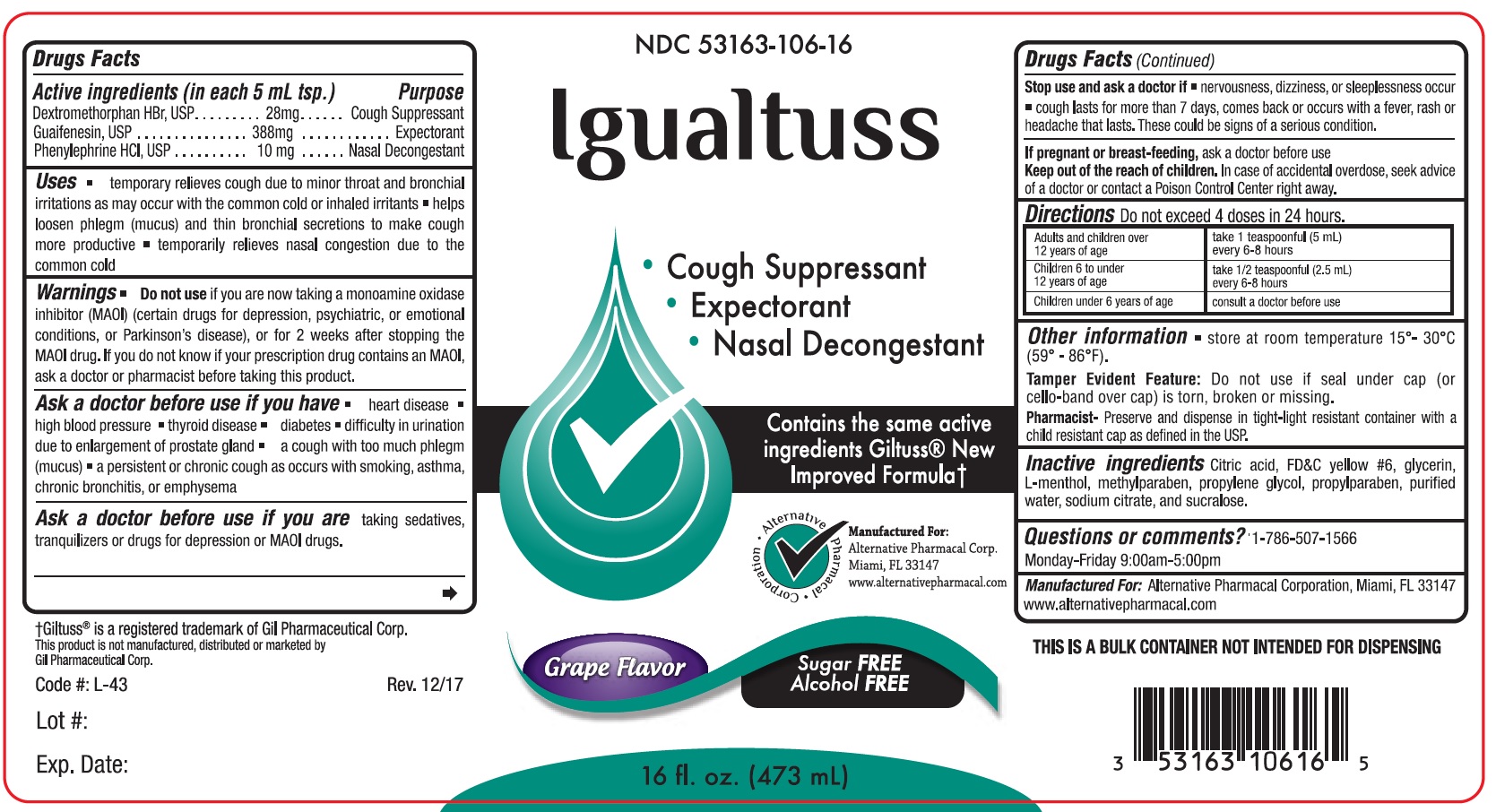 DRUG LABEL: Igualtuss
NDC: 53163-106 | Form: LIQUID
Manufacturer: Alternative Pharmacal Corporation
Category: otc | Type: HUMAN OTC DRUG LABEL
Date: 20241223

ACTIVE INGREDIENTS: DEXTROMETHORPHAN HYDROBROMIDE 28 mg/5 mL; GUAIFENESIN 388 mg/5 mL; PHENYLEPHRINE HYDROCHLORIDE 10 mg/5 mL
INACTIVE INGREDIENTS: SUCRALOSE; CITRIC ACID MONOHYDRATE; MENTHOL; METHYLPARABEN; GLYCERIN; PROPYLPARABEN; WATER; SODIUM CITRATE; FD&C YELLOW NO. 6

Alt-Igualtuss 106

Active Ingredients (in each 5 mL tsp.) Purpose

Dextromethorphan HBr ............... 28 mg ................ Cough Suppressant

Guaifenesin .............................. 388 mg ................ Expectorant

Phenylephrine HCl ..................... 10 mg ................... Nasal Decongestant

Purpose

Cough Suppressant

Expectorant

Nasal Decongestant

Warnings

Do not use if you are now taking a prescription Monoamine Oxidase Inhibitor (MAOI) (certain drugs for depression, psychiatric or emotional conditions or Parkinson's disease), or for 2 weeks after stopping the MAOI drug. If you do not know if you are taking a prescription drug that contains an MAOI; ask your doctor or pharmacist before taking this product.

Ask a doctor before use if you have

- heart disease
- high blood pressure
- thyroid disease
- diabetes
- difficulty in urination due to enlargement of prostate gland
- a cough with too much phlegm (mucus)
- a persistent or chronic cough as occurs with smopking, asthma, chronic bronchitis, or emphysema

Ask a doctor before use if you are taking sedatives, tranquilizers or drugs for depression or MAOI drugs.

Stop use and ask a doctor if

- nervousness, dizziness, or sleeplessness occur
- cough lasts for more than 7 days, comes back or occurs with a fever, rash or headache that lasts. These could be signs of serious condition.

PREGNANCY OR BREAST FEEDING

If pregnant or breast-feeding,ask a doctor before use.

Keep out of reach of children.In case of accidental overdose, seek advice of a doctor or contact a Poison Control Center right away.

Uses

- temporarily relieves cough due to minor throat and bronchial irritations as may occur with the common cold or inhaled irritants
- helps loosen phlegm (mucus) and thin bronchial secretions to make cough more productive
- temporarily releives nasal congestion due to the common cold.

DOSAGE AND ADMINISTRATION

Directions Do not exceed more than 4 doses in 24 hours.

Adults and children over 12 years of age take 1 teaspoonful (5 mL) every 6-8 hours

Children 6 to under 12 years of age take 1/2 teaspoonful (2.5 mL) every 6-8 hours

Children under 6 years of age consult a doctor before use

INACTIVE INGREDIENT

Inactive ingredients:Citric acid, FD&C Yellow #6, glycerin, menthol, methylparaben, propylene glycol, propylparaben, purified water, sodium citrate, and sucralose

Questions or comments?1-786-507-1566

Monday-Friday 9:00AM -5:00PM